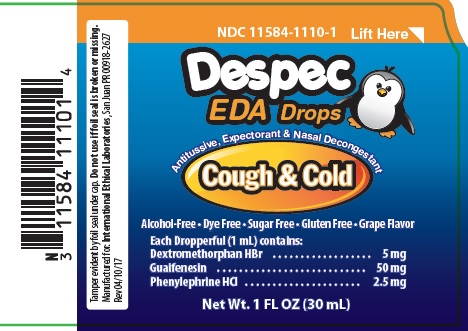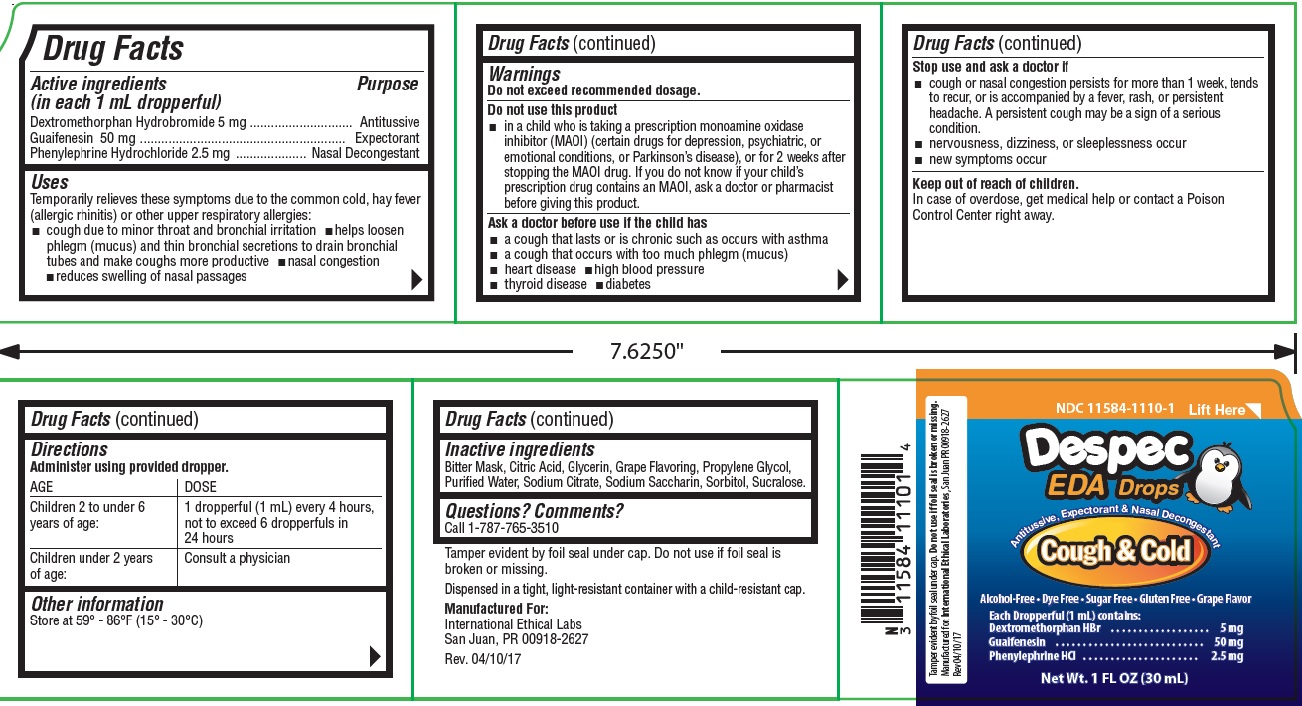 DRUG LABEL: Despec
NDC: 11584-1110 | Form: LIQUID
Manufacturer: International Ethical Labs
Category: otc | Type: HUMAN OTC DRUG LABEL
Date: 20181015

ACTIVE INGREDIENTS: DEXTROMETHORPHAN HYDROBROMIDE 5 mg/1 mL; GUAIFENESIN 50 mg/1 mL; PHENYLEPHRINE HYDROCHLORIDE 2.5 mg/1 mL
INACTIVE INGREDIENTS: CITRIC ACID MONOHYDRATE; GLYCERIN; PROPYLENE GLYCOL; WATER; SODIUM CITRATE; SACCHARIN SODIUM; SORBITOL; SUCRALOSE

Despec EDA Drops

ACTIVE INGREDIENT

Active ingredients:
(in each 1 mL dropperful)
Dextromethorphan Hydrobromide 5 mg
Guaifenesin 50 mg
Phenylephrine Hydrochloride 2.5 mg

PURPOSE

Antitussive
Expectorant
Nasal Decongestant

INDICATIONS & USAGE

Uses:

Temporarily relieves these symptoms due to the common cold, hay fever (allergic

rhinitis) or other upper respiratory allergies:

-cough due to minor throat and bronchial irritation

-helps loosen phlegm (mucus) and thin bronchial secretions to drain bronchial tubes and make coughs more productive

-nasal congestion reduces swelling of nasal passages

WARNINGS

Do not exceed recommended dosage.

Do not use this product

in a child who is taking a prescription monoamine oxidase inhibitor (MAOI) (certain drugs for depression, psychiatric, or emotional conditions, or Parkinson's disease), or for 2 weeks after stopping the MAOI drug. If you do not know if your child's prescription drug contains an MAOI, ask a doctor or pharmacist before giving this product.

ASK DOCTOR

Ask a doctor before use if the child has:

a cough that lasts or is chronic such as occurs with asthma
a cough that occurs with too much phlegm (mucus)
heart disease
high blood pressure
thyroid disease
diabetes

STOP USE

Stop use and ask a doctor if:

cough or nasal congestion persists for more than 1 week, tends to recur, or is accompanied by a fever, rash, or persistent headache. A persistent cough may be a sign of a serious condition.
nervousness, dizziness, or sleeplessness occur

new symptoms occur

KEEP OUT OF REACH OF CHILDREN

In case of overdose, get medical help or contact a Poison Control Center right away.

DOSAGE & ADMINISTRATION

Directions:

Administer using provided dropper.

AGE

DOSE

Children 2 to under
6 years of age:

1 dropperful (1 mL) every 4 hours,
not to exceed 6 dropperfuls in 24
hours

Children under 2 years of age:

Consult a physician

INACTIVE INGREDIENT

Inactive ingredients:

Bitter Mask, Citric Acid, Glycerin, Grape Flavoring, Propylene Glycol, Purified Water, Sodium Citrate, Sodium Saccharin, Sorbitol, Sucralose.

OTHER SAFETY INFORMATION

Other information:

Store at 59° - 86°F (15° - 30°C)

QUESTIONS

Questions? Comments?

Call 1-787-765-3510

Tamper evident by foil seal under cap. Do not use if foil seal is broken or missing.
Dispensed in a tight, light-resistant container with a child-resistant cap.
Manufactured For:
International Ethical Labs
San Juan, PR 00918-2627
Rev. 04/10/17